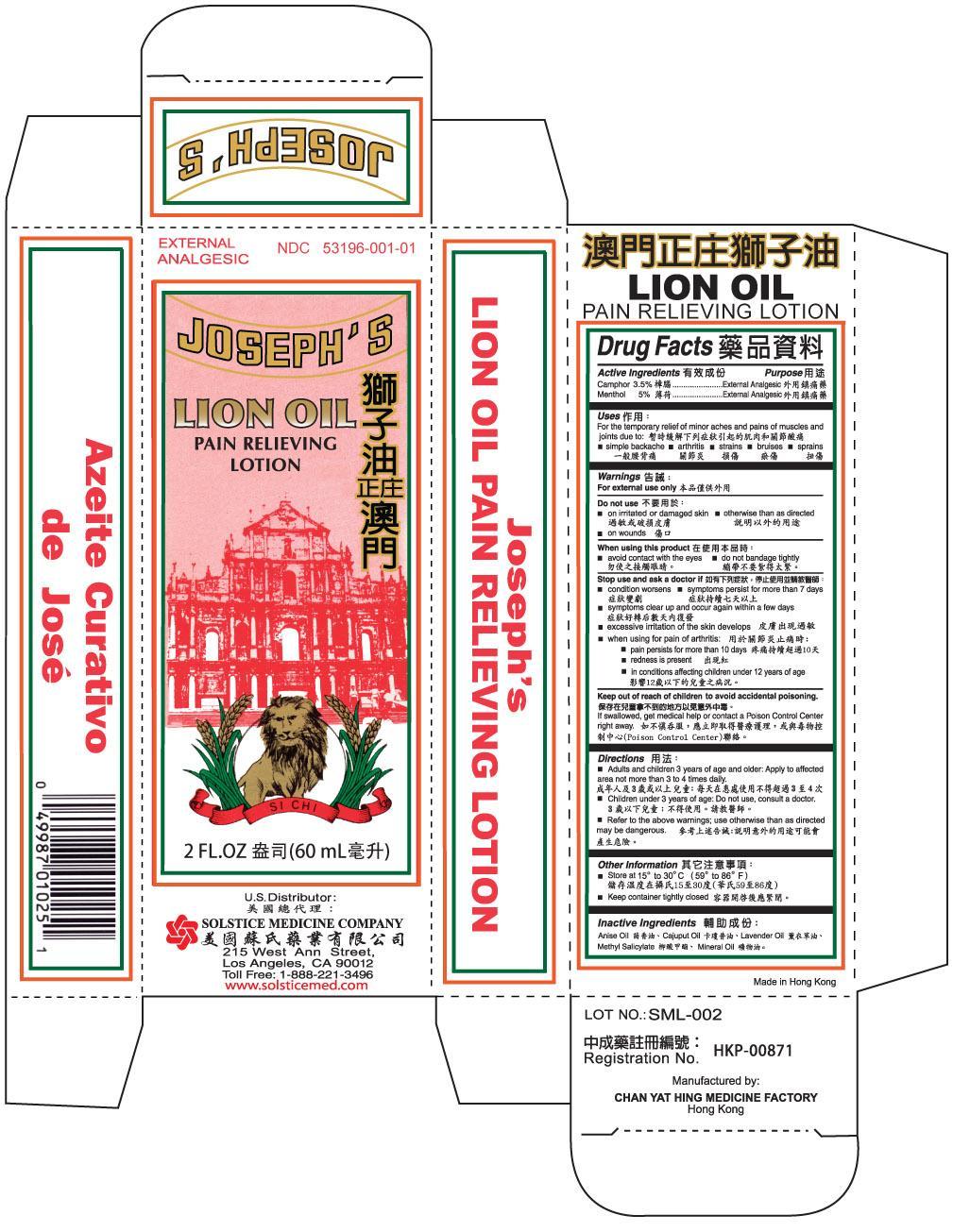 DRUG LABEL: JOSEPHS LION
NDC: 53196-001 | Form: LOTION
Manufacturer: CHAN YAT HING MEDICINE FACTORY
Category: otc | Type: HUMAN OTC DRUG LABEL
Date: 20191114

ACTIVE INGREDIENTS: CAMPHOR (SYNTHETIC) 3.5 g/100 mL; MENTHOL 5 g/100 mL
INACTIVE INGREDIENTS: ANISE OIL; CAJUPUT OIL; LAVENDER OIL; METHYL SALICYLATE; MINERAL OIL

DRUG FACTS

Active ingredients
Camphor 3.5%
Menthol 5%

Purpose
External analgesic

Warnings
For external use only

Do not use

- on wounds
- on irritated or damaged skin
- otherwise than as directed

When using this product

- avoid contact with the eyes or mucous membranes
- do not bandage tightly

Stop use and ask a doctor if

- condition worsens
- symptoms persist for more than 7 days
- symptoms clear up and occur again within a few days
- excessive irritation of the skin develops

when using for pain of arthritis:

- pain persists for more than 10 days
- redness is present
- in conditions affecting children under 12 years of age

Keep out of reach of children to avoid accidental poisoning.
If swallowed, get medical help or contact a Poison Control Center right away.

Directions

- adults and children 3 years of age and older: apply to affected area not more than 3 to 4 times daily.
- children under 3 years of age: do not use, consult a physician.
- refer to the above warnings; use otherwise than as directed may be dangerous.

Other information
keep container tightly closed
store at 15E to 30 C (59 to 86 F)

Inactive ingredients
Anise oil, cajuput oil, lavender oil, methyl salicylate,and mineral oil.

Questions or comments? (888) 221-3496 M-F 9 am to 5 pm

Uses
For the temporary relief of minor aches and pains of muscles and joints due to:
simple backache, arthritis, strains, bruises, sprains

PACKAGE LABEL

JOSEPH’S LION OIL, PAIN RELIEVING LOTION, NDC 53196-001-01, 2 fl oz (60 mL)